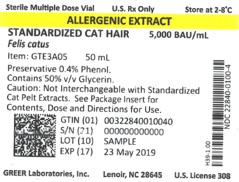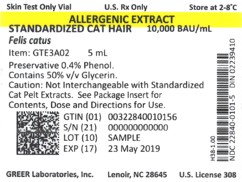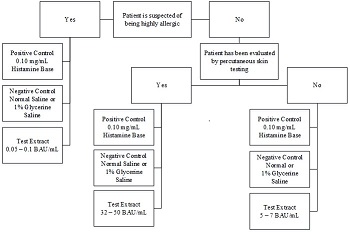 DRUG LABEL: Standardized Cat Hair Allergenic Extract
NDC: 22840-0100 | Form: SOLUTION
Manufacturer: Greer Laboratories, Inc.
Category: other | Type: STANDARDIZED ALLERGENIC
Date: 20250206

ACTIVE INGREDIENTS: FELIS CATUS DANDER 5000 [BAU]/1 mL; FELIS CATUS SKIN 5000 [BAU]/1 mL
INACTIVE INGREDIENTS: GLYCERIN; SODIUM BICARBONATE; PHENOL; SODIUM CHLORIDE

HIGHLIGHTS OF PRESCRIBING INFORMATION

ALLERGENIC EXTRACT STANDARDIZED - CAT HAIR, Felis catus Solution for percutaneous, intradermal, or subcutaneous administration
These highlights do not include all the information needed to use Standardized Cat Hair Allergenic Extract safely and effectively. See full prescribing information for Standardized Cat Hair Allergenic Extract.
Standardized Cat Hair Allergenic Extract (Felis catus) solution for percutaneous, intradermal, or subcutaneous administration.
Initial U.S. Approval: 1992

WARNING: SEVERE ALLERGIC REACTIONS

See full prescribing information for complete boxed warning.

- Cat Hair allergenic extract can cause severe life-threatening systemic reactions, including anaphylaxis. (5.1)
- Do not administer Cat Hair allergenic extract to patients with severe, unstable or uncontrolled asthma. (4)
- Observe patients in the office for at least 30 minutes following treatment. Emergency measures and personnel trained in their use must be available immediately in the event of a life-threatening reaction. (5.1)
- Patients with extreme sensitivity, on an accelerated immunotherapy build-up, switching to another lot, or receiving high doses of Cat Hair extract, or those also exposed to similar allergens may be at increased risk of a severe allergic reaction. (5.1)
- Cat Hair allergenic extract may not be suitable for patients with certain underlying medical conditions that may reduce their ability to survive a systemic reaction, or who are receiving beta blockers as they may be unresponsive to epinephrine. (5.1,5.2)
- Cat Hair extracts with potency labeling in Bioequivalent Allergy Units/milliliter is not interchangeable with Cat Pelt extracts labeled in Bioequivalent Allergy Units/milliliter. (5.3)

1 Indications and Usage

GREER Standardized Cat Hair Allergenic Extract is indicated for:

- Skin test diagnosis of patients with a history of allergy to cats. (1)
- Treatment of cat hair-induced allergic asthma, rhinitis and conjunctivitis when avoidance is not possible. (1)

2 DOSAGE AND ADMINISTRATION

For percutaneous, intradermal or subcutaneous use only.

The extract is diluted with sterile diluents when used for intradermal testing or subcutaneous immunotherapy. Dosages vary by mode of administration, and by individual response and tolerance. (2.1)

3 DOSAGE FORMS AND STRENGTHS

Stock concentrate vials at 10,000 and 5,000 Bioequivalent Allergy Units/milliliter. (3)

4 CONTRAINDICATIONS

- Severe, unstable or uncontrolled asthma. (4)
- History of any severe systemic allergic reaction or any severe local reaction to subcutaneous allergen immunotherapy. (4)

5 WARNINGS AND PRECAUTIONS

Severe allergic reactions have occurred following the administration of other allergenic extracts and may occur in individuals following the administration of Cat Hair allergenic extract in the following situations:

- Extreme sensitivity to cat hair, or receiving high doses of Cat Hair extract or concomitant exposure to similar environmental allergens. (5.1)
- Receiving an accelerated immunotherapy build-up schedule (e.g., “rush” immunotherapy), or changing from one allergenic lot to another. (5.1)

6 ADVERSE REACTIONS

The most common adverse reactions, occuring in over 25% of all patients, are local reactions at the injection site (e.g., erythema, itching, swelling, tenderness, pain). (6)
Systemic reactions, occurring in ≤ 7% of patients, include generalized skin erythema, urticaria, pruritus, angioedema, rhinitis, wheezing, laryngeal edema, and hypotension. These can be fatal. (6)
To report SUSPECTED ADVERSE REACTIONS, contact GREER Laboratories, Inc. at 1-800-438-0088 or FDA at 1-800-FDA-1088 or www.fda.gov/medwatch.

7 DRUG INTERACTIONS

- Beta blockers may cause unresponsiveness to usual doses of epinephrine used to treat serious systemic reactions, including anaphylaxis. (7.1)
- Antihistamines and other medications that suppress histamine, including topical corticosteroids, topical anesthetics and tricyclic antidepressants can interfere with skin test results. (7.2)

FULL PRESCRIBING INFORMATION

WARNING: SEVERE ALLERGIC REACTIONS

- Cat Hair allergenic extract can cause severe life‑threatening systemic reactions, including anaphylaxis. (5.1)
- Do not administer Cat Hair allergenic extract to patients with severe, unstable, or uncontrolled asthma. (4)
- Observe patients in the office for at least 30 minutes following treatment. Emergency measures and personnel trained in their use must be available immediately in the event of a life-threatening reaction. (5.1)
- Patients with extreme sensitivity to Cat Hair allergenic extract, those on an accelerated immunotherapy build-up schedule, switching to another allergenic lot, and those receiving high doses of the Cat Hair allergenic extract or are also exposed to similar allergens may be at increased risk of a severe allergic reaction. (5.1)
- Cat Hair allergenic extract may not be suitable for patients with certain underlying medical conditions that may reduce their ability to survive a systemic reaction. (5.1)
- Cat Hair allergenic extract may not be suitable for patients who are receiving beta blockers as they may be unresponsive to epinephrine. (5.2)
- Standardized Cat Hair Allergenic Extract with potency labeling in Bioequivalent Allergy Units/milliliter is not interchangeable with Standardized Cat Pelt Allergenic Extracts labeled in Bioequivalent Allergy Units/milliliter. (5.3)

1 Indications and Usage

GREER Standardized Cat Hair Allergenic Extract is indicated for:

- Skin test diagnosis of patients with a history of allergy to cats.
- Treatment of cat hair-induced allergic asthma, rhinitis and conjunctivitis. Immunotherapy is indicated when cat allergy is established and the patient cannot avoid exposure to cat allergens.

2 DOSAGE AND ADMINISTRATION

For percutaneous, intradermal or subcutaneous use only.

Stock concentrate vials are available at 10,000 and 5,000 Bioequivalent Allergy Units (BAU)/milliliter.

2.1 Preparation for Administration

Visually inspect parenteral drug products for particulate matter and discoloration prior to administration, whenever solution and container permit. GREER Standardized Cat Hair Allergenic Extract should be a clear and colorless to light yellow solution that is free of particulate matter. Discard solution if particulate matter is observed.

The extracts are diluted with sterile diluents when used for percutaneous and intradermal testing, or for subcutaneous immunotherapy.

To prepare 10-fold dilutions for percutaneous testing in highly sensitive patients, start with a 10,000 BAU/milliliter or 5,000 BAU/milliliter stock concentrate. Proceed as in Table 1. The 10-fold dilution series uses 0.5 milliliters of concentrate added to 4.5 milliliters of sterile 50% glycerin diluent. Subsequent dilutions are made in a similar manner.

To prepare 10-fold dilutions for intradermal testing or immunotherapy, start with a 10,000 BAU/milliliter or 5,000 BAU/milliliter stock concentrate. Proceed as in Table 1. The 10-fold dilution series uses 0.5 milliliters of concentrate added to 4.5 milliliters of sterile diluent (glycerin-free diluents for intradermal testing, glycerin-free or 10% glycerin-saline diluents for immunotherapy). Subsequent dilutions are made in a similar manner.

Table 1: 10-fold Dilution Series
Dilution | Extract | Milliliters of Diluent | BAU/milliliter | BAU/milliliter
0 | Concentrate |  | 10,000 | 5,000
1 | 0.5 milliliters Concentrate | 4.5 | 1,000 | 500
2 | 0.5 milliliters Dilution 1 | 4.5 | 100 | 50
3 | 0.5 milliliters Dilution 2 | 4.5 | 10 | 5
4 | 0.5 milliliters Dilution 3 | 4.5 | 1 | 0.5
5 | 0.5 milliliters Dilution 4 | 4.5 | 0.1 | 0.5
6 | 0.5 milliliters Dilution 5 | 4.5 | 0.01 | 0.005

To prepare 5-fold dilutions for percutaneous testing in highly sensitive patients, start with a 10,000 BAU/milliliter or 5,000 BAU/milliliter stock concentrate. Proceed as in Table 2. The 5-fold dilution series uses 1 milliliter of concentrate added to 4 milliliters of sterile 50% glycerin diluent. Subsequent dilutions are made in a similar manner.

To prepare 5-fold dilutions for intradermal testing or immunotherapy, start with a 10,000 BAU/milliliter or 5,000 BAU/milliliter stock concentrate. Proceed as in Table 2. The 5-fold dilution series uses 1 milliliter of concentrate added to 4 milliliters of sterile diluent (glycerin-free diluents for intradermal testing, glycerin-free or 10% glycerin-saline diluents for immunotherapy). Subsequent dilutions are made in a similar manner.

Table 2: 5-fold Dilution Series
Dilution | Extract | Milliliters of Diluent | BAU/milliliter | BAU/milliliter
0 | Concentrate |  | 10,000 | 5,000
1 | 1 milliliters Concentrate | 4 | 2,000 | 1,000
2 | 1 milliliters Dilution 1 | 4 | 400 | 200
3 | 1 milliliters Dilution 2 | 4 | 80 | 40
4 | 1 milliliters Dilution 3 | 4 | 16 | 8
5 | 1 milliliters Dilution 4 | 4 | 3.2 | 1.6
6 | 1 milliliters Dilution 5 | 4 | 0.64 | 0.32

2.2 Diagnostic Testing

Diagnostic testing can be performed via percutaneous or intradermal administration of the Cat Hair allergenic extract. A positive skin test reaction must be interpreted in relation to the patient’s history and known exposure to the allergen.

Percutaneous Skin Testing

Determine the patient’s sensitivity to the Standardized Cat Hair Allergenic Extract.

Prick or puncture testing: use 10,000 BAU/milliliter or 5,000 BAU/milliliter extract stock concentrate.

In highly sensitive patients initiate testing with several serial 10-fold or 5-fold dilutions.

Preparation and Dose
For percutaneous testing (prick or puncture) use 10,000 or 5,000 BAU/milliliter stock concentrates. If a lower concentration is desired in highly sensitive patients, 10-fold or 5-fold dilutions of the concentrate can be tested.

Prick test: Place one drop of extract or control on the skin and with a skin test device pierce through the drop into the skin with a slight lifting motion.

Puncture test: Place one drop of extract or control on the skin and pierce the skin through the drop with a skin test device perpendicular to the skin.

Interpreting Results
When using percutaneous skin test devices, follow the directions provided with the test devices. A glycerinated histamine control solution (6 milligrams/milliliter or 1 milligram/milliliter histamine base) may be used as the positive control. A 50% glycerin saline solution may be used as the negative control.

Read skin test responses 15 to 20 minutes after exposure and measure the average diameter of the induration (wheal) and erythema (flare), or the sum of the longest diameter and the mid-point orthogonal diameters of erythema (ΣE).

An example of a commonly used scale is provided in Table 3 below.^1,2

Table 3: Grading Sensitivity
Grade | Skin Apperarance
0 | No reaction or reaction no different than negative control
1+ | Erythema less than 21 milliliters
2+ | Wheal less than 3 milliliters and erythema larger than 21 milliliters
3+ | Wheal greater than 3 milliliters with surrounding erythema
4+ | Wheals with pseudopods and surrounding erythema

Responses to positive controls should be at least 3 millimeters larger than responses to the negative controls.

Negative controls should elicit no reaction or only reactions of small diameters (less than 2 millimeters wheal, less than 5 millimeters erythema).

If either the positive or negative control response does not meet the above criteria, results for the allergenic extracts tested at the same time are invalid and must be repeated.

Intradermal Skin Testing

For intradermal testing, use 10,000 BAU/milliliter or 5,000 BAU/milliliter of GREER Standardized Cat Hair Allergenic Extract stock concentrate in 10, 30 or 50 milliliters multiple-dose vials. Dilute the stock concentrate with sterile diluent [see Dosage and Administration (2.1)]. Use normal or buffered saline or normal saline with human serum albumin (HSA) diluent. If the initial test dose is negative, subsequent intradermal tests using increasingly stronger doses may be performed up to the maximum recommended strength of 200 BAU/milliliter.

Preparation and Dose
Inject 0.02 milliliters of the following solutions intradermally as shown in Figure 1:

Figure 1: Conditions of Testing

2.3 Immunotherapy

For subcutaneous administration only.

Preparation and Dose

Stock concentrate of GREER Standardized Cat Hair Allergenic Extract is available at 10,000 BAU/milliliter or 5,000 BAU/milliliter in 50% glycerin saline for immunotherapy. Stock concentrates are diluted in normal saline, buffered saline, HSA saline, or 10% glycerin saline, depending on the patient’s reactivity to the diluent. See Table 1 and Table 2 for dilution preparation.

Administration of Immunotherapy

Administer immunotherapy by subcutaneous injection in the lateral aspect of the upper arm or thigh. Avoid injection directly into any blood vessel.

The optimal interval between doses of allergenic extract varies among individuals. Injections are usually given 1 to 2 times per week until the maintenance dose is reached, at which time the injection interval is increased to 2, then 3, and finally 4 weeks. Dosages vary by mode of administration, and by clinical response and tolerance. The minimum course of treatment may be three to five years, depending on the clinical response.

Guidelines for Immunotherapy

The initial dose of the extract should be based on the skin test reactivity. In patients who appear to be highly sensitive by history and skin test, the initial dose of the extract should be 0.1 milliliter of a 0.005 to 0.05 BAU/milliliter extract dilution. Patients with lesser sensitivity may be started at a 0.1 milliliter of a 0.5 to 5 BAU/milliliter extract dilution.

The dose of allergenic extract is increased at each injection by no more than 50% of the previous dose, and the next increment is governed by the response to the last injection.

Select the maximum tolerated maintenance dose based on the patient's clinical response and tolerance. Doses larger than 0.2 milliliter of the stock concentrate are rarely administered because an extract in 50% glycerin can cause discomfort upon injection.

Dosage Modification Guidelines for Immunotherapy

The following conditions may indicate a need to withhold or reduce the dosage of immunotherapy.

Symptoms of rhinitis and/or asthma.

Infection accompanied by fever.

Exposure to excessive amounts of clinically relevant environmental allergen prior to a scheduled injection.

Large local reactions that persist for longer than 24 hours can be an indication for repeating the previous dose or reducing the dose at the next administration.

Any evidence of a systemic reaction is an indication for a significant reduction (at least 75%) in the subsequent dose. Repeated systemic reactions, are sufficient reason for the cessation of further attempts to increase the reaction-causing dose.

Local reactions require a decrease in the next dose by at least 50%. Proceed cautiously in subsequent dosing. In situations prompting dose reduction, once the reduced dose is tolerated, a cautious increase in dosage can be attempted.

Changing to a different lot of extract: When switching patients to different lot of extract, the first dose from the new vial should not exceed a 25% increase of the previous dose or a 75% reduction of the previous dose, assuming both extracts contain comparable amounts of allergen as measured in BAU/milliliter.

Unscheduled gaps between treatments: Patients can lose tolerance for allergen injections during prolonged periods between doses, thus increasing their risk for an adverse reaction. The duration of tolerance between injections varies from patient to patient.

During the build-up phase, when patients receive injections 1 to 2 times per week, repeat or reduce the extract dosage if there has been a substantial time interval between injections. This depends on: 1) the concentration of allergen immunotherapy extract that is to be administered; 2) a previous history of systemic reactions; and 3) the degree of variation from the prescribed interval of time, with longer intervals since the last injection leading to greater reductions in the dose to be administered. This suggested approach to dose modification, due to unscheduled gaps between treatments during the build-up phase, is not based on published evidence. The individual physician should use this or a similar protocol for the specific clinical setting.

Similarly, if large unscheduled gaps occur during maintenance therapy, it may be necessary to reduce the dosage. Devise a protocol for the specific clinical setting in determining how to modify doses of allergen immunotherapy due to unscheduled gaps in treatment.

Extract previously used from different manufacturer: Since manufacturing processes and sources of raw materials differ among manufacturers, the interchangeability of extracts from different manufacturers cannot be assured. Decrease the starting dose of the extract from a different manufacturer even if the extract is the same dilution. In general, a dose reduction of 50 to 75% of the previous dose should be adequate, but each situation must be evaluated separately considering the patient’s history of sensitivity, tolerance of previous injections, and other factors. Dose intervals should not exceed one week when rebuilding dose.

Changing from non-stabilized to human serum albumin (HSA) stabilized diluents: Allergenic extracts prepared with diluents containing HSA and 0.4% phenol are more stable than those prepared with diluents that do not contain stabilizers. When switching from a non-stabilized to an HSA stabilized diluent, consider lowering the dose for immunotherapy.

3 DOSAGE FORMS AND STRENGTHS

Standardized Cat Hair Allergenic Extract is supplied as stock concentrate vials at 10,000 BAU/milliliter and 5,000 BAU/milliliter.

4 CONTRAINDICATIONS

Standardized Cat Hair Allergenic Extract is contraindicated in patients with:

- Severe, unstable or uncontrolled asthma.
- History of any severe systemic allergic reaction or any severe local reaction to subcutaneous allergen immunotherapy.

5.1 Serious Systemic Reactions

Severe allergic reactions have occurred following the administration of other allergenic extracts and may occur in individuals following the administration of Standardized Cat Hair Allergenic Extract in the following situations:

- Extreme sensitivities to Cat Hair allergenic extract.
- Receiving an accelerated immunotherapy build-up schedule (e.g., “rush” immunotherapy).
- Receiving high doses of Cat Hair allergenic extracts or concomitant exposure to similar environmental allergens.
- Changing from one allergenic lot to another allergenic lot.

High-risk patients have had fatal reactions. In addition, patients who are not high-risk, but are on beta blockers, have had fatal reactions because beta blockers interfere with beta adrenergics, such as epinephrine, used in the treatment of anaphylaxis.

Administer Cat Hair Allergenic Extract in a healthcare setting under the supervision of a physician prepared to manage a severe systemic or a severe local allergic reaction. Observe patients in the office for at least 30 minutes following administration.^3

5.2 Patients on Beta Blockers

Patients receiving beta blockers may be unresponsive to the usual doses of epinephrine used to treat serious systemic reactions, including anaphylaxis [see Drug Interactions (7.1)].

5.3 Cross-Reactions and Dose Sensitivity

GREER Standardized Cat Hair Allergenic Extract is labeled in BAU/milliliter. This allergenic extract is not interchangeable with Standardized Cat Pelt Extract or with cat extracts labeled in Allergy Units.

Determine the initial dilution of allergenic extract, starting dose, and progression of dosage based on the patient’s history and results of skin tests^1 [see Dosage and Administration (2.2)]. Strongly positive skin tests can be an indicator for potential systemic reactions.

6 ADVERSE REACTIONS

Allergenic extracts including Standardized Cat Hair can cause local reactions at the injection site, which may include erythema, itching, swelling, tenderness and pain.^3 Additionally, systemic reactions, which may indicate anaphylaxis, can occur and may include generalized skin erythema, urticaria, pruritus, angioedema, rhinitis, wheezing, chest tightness, laryngeal edema and hypotension.

7.1 Beta Adrenergic Drugs

Patients receiving beta blocker drugs may not be responsive to beta adrenergic drugs used to treat anaphylaxis [see Warnings and Precautions (5.2)].

7.2 Antihistamines

Do not perform skin testing with allergenic extracts within 3 to 10 days of use of first-generation H1-histamine receptor blockers (e.g., clemastine, diphenhydramine) and second-generation antihistamines (e.g., loratadine, terfenadine), except for astemizole, which requires an interval of 30 to 60 days between use and allergenic extract exposure. These products suppress histamine skin test reactions and could mask a positive response.^1

7.3 Topical Corticosteroids and Topical Anesthetics

Topical corticosteroids can suppress skin reactivity; therefore, discontinue use at the skin test site for 2 to 3 weeks before skin testing. Avoid use of topical local anesthetics at skin test sites as they can suppress flare responses.^1

7.4 Tricyclic Antidepressants

Tricyclic antidepressants can have potent antihistamine effects that can affect skin testing. If tricyclic medication has been recently discontinued allow 7 to 14 days before initiating skin testing.

8.1 Pregnancy

Pregnancy Category C: Animal reproduction studies have not been conducted with GREER Standardized Cat Hair Allergenic Extract. It is not known whether allergenic extracts can cause fetal harm when administered to a pregnant woman or can affect reproduction capacity. Standardized Cat Hair Allergenic Extract should be given to a pregnant woman only if clearly needed. Immunotherapy is typically not initiated during pregnancy due to the risks associated with systemic reactions and their treatment.^3

8.2 Labor and Delivery

Safety and effectiveness of allergenic extracts in labor and delivery have not been established.

8.3 Nursing Mothers

It is not known whether allergenic extracts or their antigens are excreted in human milk. Because many drugs are excreted in human milk, exercise caution when administering Standardized Cat Hair Allergenic Extract to a nursing woman.

8.4 Pediatric Use

Safety and effectiveness in pediatric patients have not been established.

8.5 Geriatric Use

Safety and effectiveness of GREER Standardized Cat Hair Allergenic Extract have not been established in patients > 65 years of age.

8.6 Autoimmune Disease

For patients with existing immunologic diseases, give immunotherapy only if the risk from exposure to the allergens is greater than the risk of exacerbating the underlying disorder.^3

11 DESCRIPTION

GREER Standardized Cat Hair Allergenic Extract is a sterile solution of extracted cat pelt and cat dander. Each vial contains sterile Standardized Cat Hair Allergenic Extract at 10,000 BAU/milliliter or 5,000 BAU/milliliter, 50% glycerin volume/volume, and 0.4% phenol volume/volume (preservative). Inactive ingredients include 0.5% sodium chloride for isotonicity and 0.25% sodium bicarbonate as a buffer.

GREER Standardized Cat Hair Allergenic Extract is labeled in BAU/milliliter. This allergenic extract is not interchangeable with Standardized Cat Pelt Extract or with cat extracts labeled in Allergy Units. The extract is standardized by comparing potency of cat allergen (Fel d 1) units by radial immunodiffusion against a reference standard from the Center for Biologics Evaluation and Research (CBER) of the U.S. Food and Drug Administration (FDA).^4,5 An extract with 10.0 to 19.9 Fel d 1 units per milliliter is designated as 10,000 BAU/milliliter by the FDA based on quantitative skin testing.^4,5

12.1 Mechanism of Action

The precise mechanisms of action of allergy immunotherapy are not known.

The allergic reaction is dependent upon the presence of antigen-specific IgE antibodies that are bound to specific receptors on mast cells and basophils and has been demonstrated for cat-allergic individuals.^6 The presence of IgE antibodies on mast cells and basophils sensitizes these cells and upon interaction with the appropriate allergen-histamine and other mediators are released.^7 In the skin these mediators are responsible for the characteristic wheal and flare reaction.^8 An increase in cat antigen-specific IgG antibodies has been demonstrated as a result of immunotherapy.^9,10

14 CLINICAL STUDIES

The efficacy of immunotherapy for Type I hypersensitivity (i.e. allergy) to airborne allergens^3 including cat hair/dander has been well established. Specifically, immunotherapy for allergic sensitivity to cat hair allergens has been addressed in a 2003 Cochrane meta-analysis which included 10 randomized controlled trials of immunotherapy^11, which expanded on prior meta-analyses of the effectiveness of allergy immunotherapy in asthma.^12,13 In addition, efficacy for immunotherapy for rush or cluster protocols, in which dose escalation is compressed over days or weeks, has also been demonstrated.^14

15 REFERENCES

1. Bernstein IL, Li JT, Bernstein DI, Hamilton R, Spector SL, Tan R, et al. Allergy Diagnostic Testing: An Updated Practice Parameter. Ann Allergy Asthma Immunol. 2008; 100:S1-148.
2. McCann WA, Ownby DR. The Reproducibility of The Allergy Skin Test Scoring and Interpretation By Board-Certified/Board-Eligible Allergists. Ann Allergy Asthma Immunol. 2002; 89:368-371.
3. Cox L, Nelson H, Lockey R. Allergen Immunotherapy: A Practice Parameter Third Update. J Allergy Clin Immunol. 2011; 127:(1)S1-55.
4. Turkeltaub PC, Rastogi SC. Quantitative Intradermal Procedure for Evaluation of Subject Sensitivity to Standardized Allergenic Extracts and for Assignment of Bioequivalent Allergy Units to Reference Preparations Using the ID50EAL Method (Intradermal Dilution for 50 mm Sum of Erythema Determines Bioequivalent Allergy Units). In Methods of the Allergenic Products Testing Lab, LIB, DAPP, CBER, FDA, 1994.
5. RID assay for Fel d 1. CBER Manual of Methods: Methods of Allergenic Products Testing Laboratory. Rockville MD, Center for Biologics Evaluation and Research, Food and Drug Administration, Docket No. 4N-0012, 13-14, 1993.
6. Ohman JL, Kendall S, Lowell FC. IgE antibody to cat allergens in an allergic population. J Allergy Clin Immunol. 1977; 60:317.
7. Holgate ST, Robinson C, Church MK. Mediators of immediate hypersensitivity. In Allergy Principles and Practice, 3rd Ed., Middleton E Jr., Reed CE, Ellis EF, Adkinson NF Jr, Yunginger JW. Eds., St. Louis: C.V. Mosby. 1988; 135-178.
8. Norman PS. The clinical significance of IgE. Hosp Pract. 1975; 10:41-9.
9. Ohman JL, Marsh DG, Goldman M. Antibody responses following immunotherapy with cat pelt extract. J Allergy Clin Immunol. 1982; 69:320.
10. Løwenstein H, Graff-Lonnevig V, Hedlin G, Heilborn H, Lilja G, Norrlind K, Pegelow K-O, Sundin B. Immunotherapy with cat- and dog-dander extracts: III. Allergen-specific immunoglobulin responses in a 1-year double-blind placebo study. J Allergy Clin Immunol. 1966; 77:497-505.
11. Abramson MJ, Puy RM, Weiner JM. Allergen immunotherapy for asthma. The Cochrane Database of Systematic Reviews. 2003, Issue 4. Art. No.: CD001186. DOI: 10.1002/14651858.CD001186.
12. Abramson MJ, Puy RM, Weiner JM. Is allergen immunotherapy effective in asthma?: a meta-analysis of randomized controlled trials. Am J Respir Crit Care Med. 1995; 151:969-74.
13. Abramson MJ, Puy RM, Weiner JM. Immunotherapy in asthma: an updated systematic review. Allergy. 1999; 54:1022-1041.
14. Nanda, A, O’Connor M, Anada M, Dreskin SC, Zhang L, et al. Dose dependence and time course of the immunologic response to adminstration of standardized cat allergen extract. J Allergy Clin Immunol. 2004; 114(6):1339-44.

16.1 How Supplied

GREER Standardized Cat Hair Allergenic Extract is supplied as stock concentrate at 10,000 BAU/milliliter and 5,000 BAU/milliliter in 50% glycerin for use in percutaneous skin testing, intradermal testing, and subcutaneous immunotherapy. The 10,000 BAU/milliliter stock concentrate is available in 5, 10, 30 and 50 milliliter vials and the 5,000 BAU/milliliter in 10, 30 and 50 milliliter vials. GREER Standardized Cat Hair Allergenic Extract containing 10,000 BAU/milliliter and 5,000 BAU/milliliter in 50% Glycerin solution is supplied as follows:

NDC Number | Strength/Container
NDC 22840-0101-5 | 10,000 BAU/mL 5 mL dropper vial for prick testing
NDC 22840-0101-2 | 10,000 BAU/mL 10 mL multiple-dose vial
NDC 22840-0101-3 | 10,000 BAU/mL 30 mL multiple-dose vial
NDC 22840-0101-4 | 10,000 BAU/mL 50 mL multiple-dose vial
NDC 22840-0100-2 | 5,000 BAU/mL 10 mL multiple-dose vial
NDC 22840-0100-3 | 5,000 BAU/mL 30 mL multiple-dose vial
NDC 22840-0100-4 | 5,000 BAU/mL 50 mL multiple-dose vial

16.2 Storage and Handling

Maintain at 2 to 8 °C (36 to 46 °F) during storage and use.

Dilutions of concentrated extract result in a glycerin content of less than 50%, which can result in reduced stability. Extract dilutions at 1:100 v/v dilution of 10,000 BAU/milliliter Standardized Cat Hair Allergenic Extract stock concentrates should be kept no longer than a month, and more dilute solutions no more than a week. The potency of a dilution can be checked by skin test comparison to a fresh dilution of the extract on a known cat hair allergic patient.

17 PATIENT COUNSELING INFORMATION

Instruct patient to remain under observation in the office for 30 minutes or longer after an injection.

Caution patient that reactions can occur more than 30 minutes after skin testing or an injection.

Instruct patient to recognize the following symptoms as adverse reactions and to immediately return to the office or immediately seek other medical attention if any of these symptoms occur following skin testing or an injection:

- Unusual swelling and/or tenderness at the injection site
- Hives or itching of the skin
- Swelling of face and/or mouth
- Sneezing, coughing or wheezing
- Shortness of breath
- Nausea
- Dizziness or faintness

Manufacturer:
GREER Laboratories, Inc.
Lenoir, NC 28645 U.S.A.

16001015